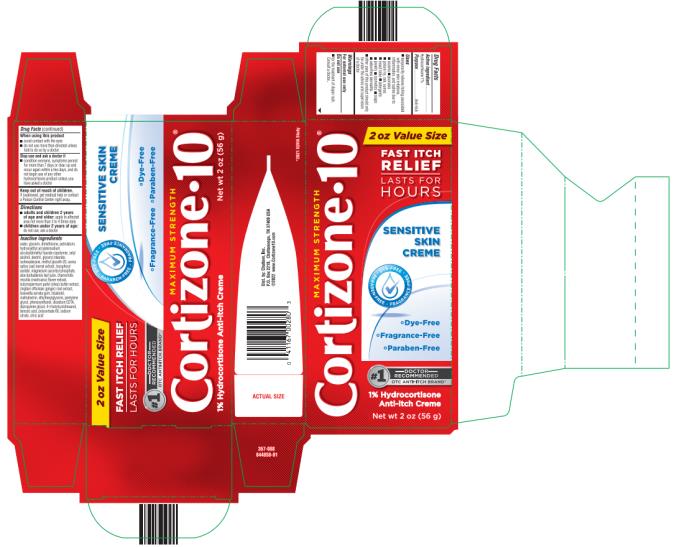 DRUG LABEL: Cortisone 10 Sensitive Skin Creme
NDC: 41167-0028 | Form: CREAM
Manufacturer: Chattem, Inc.
Category: otc | Type: HUMAN OTC DRUG LABEL
Date: 20231106

ACTIVE INGREDIENTS: HYDROCORTISONE 1 g/100 g
INACTIVE INGREDIENTS: WATER; GLYCERIN; DIMETHICONE; PETROLATUM; HYDROXYETHYL ACRYLATE/SODIUM ACRYLOYLDIMETHYL TAURATE COPOLYMER (100000 MPA.S AT 1.5%); CETYL ALCOHOL; GLYCERYL MONOSTEARATE; ISOHEXADECANE; METHYL GLUCETH-20; OAT; .ALPHA.-TOCOPHEROL ACETATE; MAGNESIUM ASCORBYL PHOSPHATE; ALOE VERA LEAF; CHAMOMILE; SHEA BUTTER; GINGER; INDIAN FRANKINCENSE; LEVOMENOL; MALTODEXTRIN; ETHYLHEXYLGLYCERIN; PENTYLENE GLYCOL; PHENOXYETHANOL; EDETATE DISODIUM ANHYDROUS; DIPROPYLENE GLYCOL; 4-TERT-BUTYLCYCLOHEXANOL; BENZOIC ACID; POLYSORBATE 60; SODIUM CITRATE; CITRIC ACID MONOHYDRATE

Cortizone 10 Sensitive Skin Creme

Cortizone 10

Sensitive Skin Anti-itch Creme

Drug Facts

Purpose

Hydrocortisone 1%...........................................................................................................................................Anti-itch

Uses

■ temporarily relieves itching associated with minor skin irritations, inflammation, and rashes due to:

■ eczema ■ psoriasis ■ poison ivy, oak, sumac ■ insect bites ■ detergents ■ jewelry ■ cosmetics

■ soaps ■ seborrheic dermatitis

■ other uses of this product should only be under the advice and supervision of a doctor

Warnings

For external use only

Do not use

■ for the treatment of diaper rash. Consult a doctor.

When using this product

■ avoid contact with the eyes

■ do not use more than directed unless told to do so by a doctor

Stop use and ask a doctor if

■ condition worsens, symptoms persist for more than 7 days or clear up and occur again within a few days, and do not begin use of any other hydrocortisone product unless you have asked a doctor

Keep out of reach of children.

If swallowed, get medical help or contact a Poison Control Center right away.

Directions

■ adults and children 2 years of age and older: apply to affected area not more than 3 to 4 times daily

■ children under 2 years of age: do not use, ask a doctor

Inactive ingredients

water, glycerin, dimethicone, petrolatum, hydroxyethyl acrylate/sodium acryloyldimethyl taurate copolymer, cetyl alcohol, dextrin, glyceryl stearate, isohexadecane, methyl gluceth-20, avena sativa (oat) kernel extract, tocopheryl acetate, magnesium ascorbyl phosphate, aloe barbadensis leaf juice, chamomilla recutita (matricaria) flower extract, butyrospermum parkii (shea) butter extract, zingiber officinale (ginger) root extract, boswellia serrata gum, bisabolol, maltodextrin, ethylhexylglycerin, pentylene glycol, phenoxyethanol, disodium EDTA, dipropylene glycol, 4-t-butylcyclohexanol, benzoic acid, polysorbate 60, sodium citrate, citric acid

PRINCIPAL DISPLAY PANEL

Cortizone 10

Sensitive Skin Crème
Net wt 2 oz (56 g)